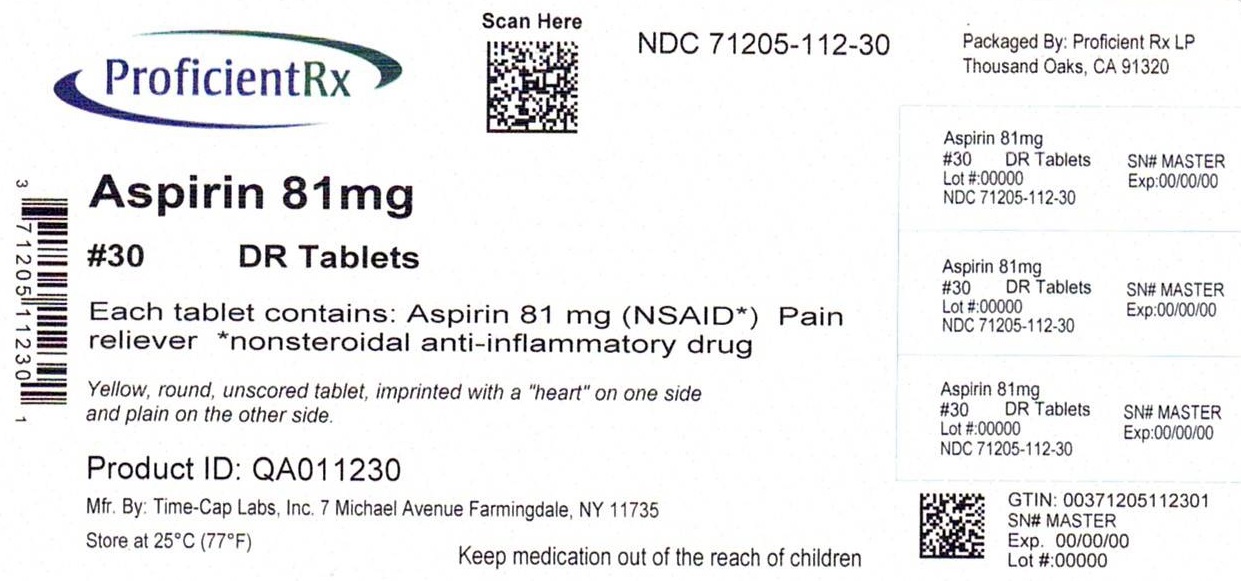 DRUG LABEL: LOW DOSE ASPIRIN
NDC: 71205-112 | Form: TABLET, COATED
Manufacturer: Proficient Rx LP
Category: otc | Type: HUMAN OTC DRUG LABEL
Date: 20241001

ACTIVE INGREDIENTS: ASPIRIN 81 mg/1 1
INACTIVE INGREDIENTS: CARNAUBA WAX; SILICON DIOXIDE; D&C YELLOW NO. 10; FERRIC OXIDE YELLOW; METHACRYLIC ACID AND ETHYL ACRYLATE COPOLYMER; POLYSORBATE 80; DIMETHICONE; SODIUM LAURYL SULFATE; STARCH, CORN; TALC; TITANIUM DIOXIDE; TRIETHYL CITRATE

481R-TCL-49483-481 ASPIRIN 81MG DELAYED RELEASE TABLETS

Active ingredient (in each tablet)

Aspirin 81mg (NSAID*)

*nonsteroidal anti-inflammatory drug

Purpose

Pain Reliever

Keep out of reach of children. In case of overdose get medical help or contact a poison control center right away.

Uses

for the temporary relief of minor aches and pains or as recommended by your doctor Because of its delayed action, this product will not provide fast relief of headaches or other symptoms needing immediate relief.
ask your doctor about other uses for enteric-coated 81 mg Aspirin

Warnings

Reye’s syndrome: Children and teenagers who have or are recovering from chicken pox or flu-like symptoms should not use this product. When using this product, if changes in behavior with nausea and vomiting occur, consult a doctor because these symptoms could be an early sign of Reye’s syndrome, a rare but serious illness.

Allergy alert: Aspirin may cause a severe allergic reaction which may include:hives, facial swelling, shock, asthma(wheezing).

Stomach bleeding warning: This product contains an NSAID which may cause severe stomach bleeding. The chance is higher if:

You are age 60 or older

Have had stomach bleeding problems

Take a blood thinning (anticoagulant) or steroid drug

Take other drugs containing prescription or nonprescription NSAIDs (aspirin, ibuprofen, naproxen or others)

Directions

Drink a full glass of water with each dose

Adults and children of 12 years and over, take 4-8 tablets every 4 hours not to exceed 48 tablets in 24 hours unless directed by a doctor

Children under 12 years: consult a doctor

Inactive Ingredients

Anhydrous lactose, carnuba wax, colloidal silicon dioxide, croscarmellose sodium, D&C yellow #10 aluminum lake, iron oxide ochre, methacrylic acid copolymer, microcrystalline cellulose, polysorbate 80, simethicone, sodium hydroxide, sodium lauryl sulfate, talc, titanium dioxide, triethyl citrate.